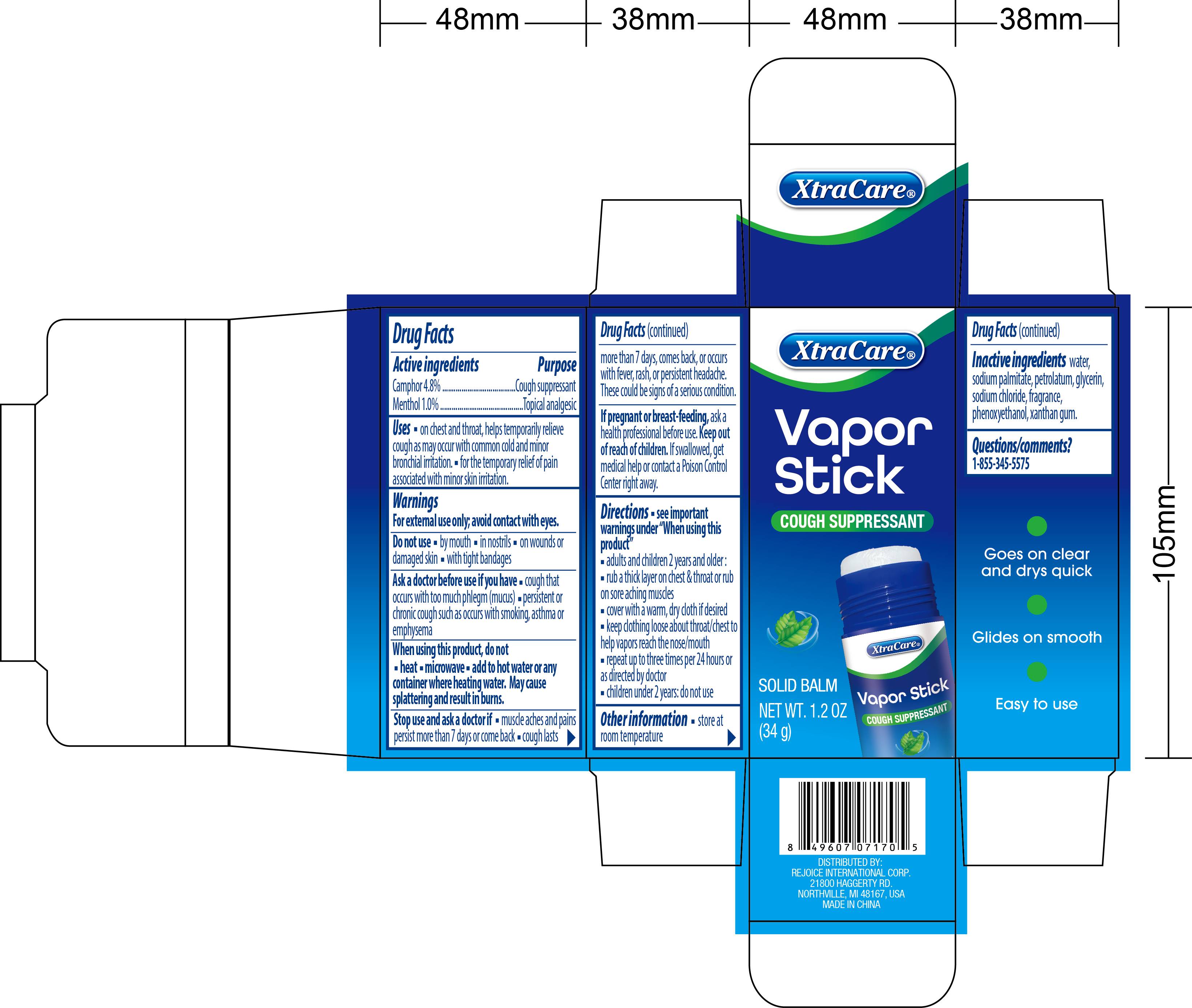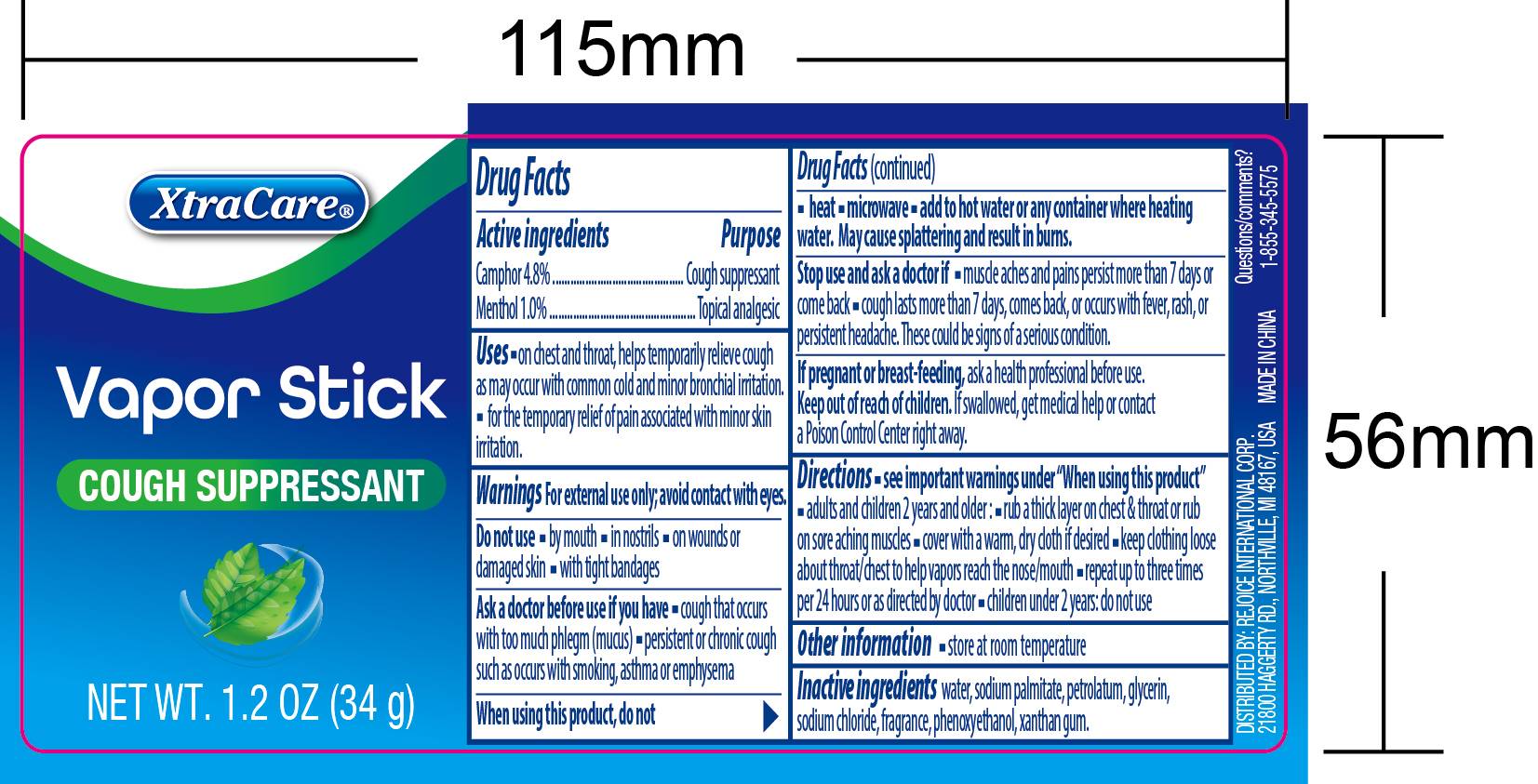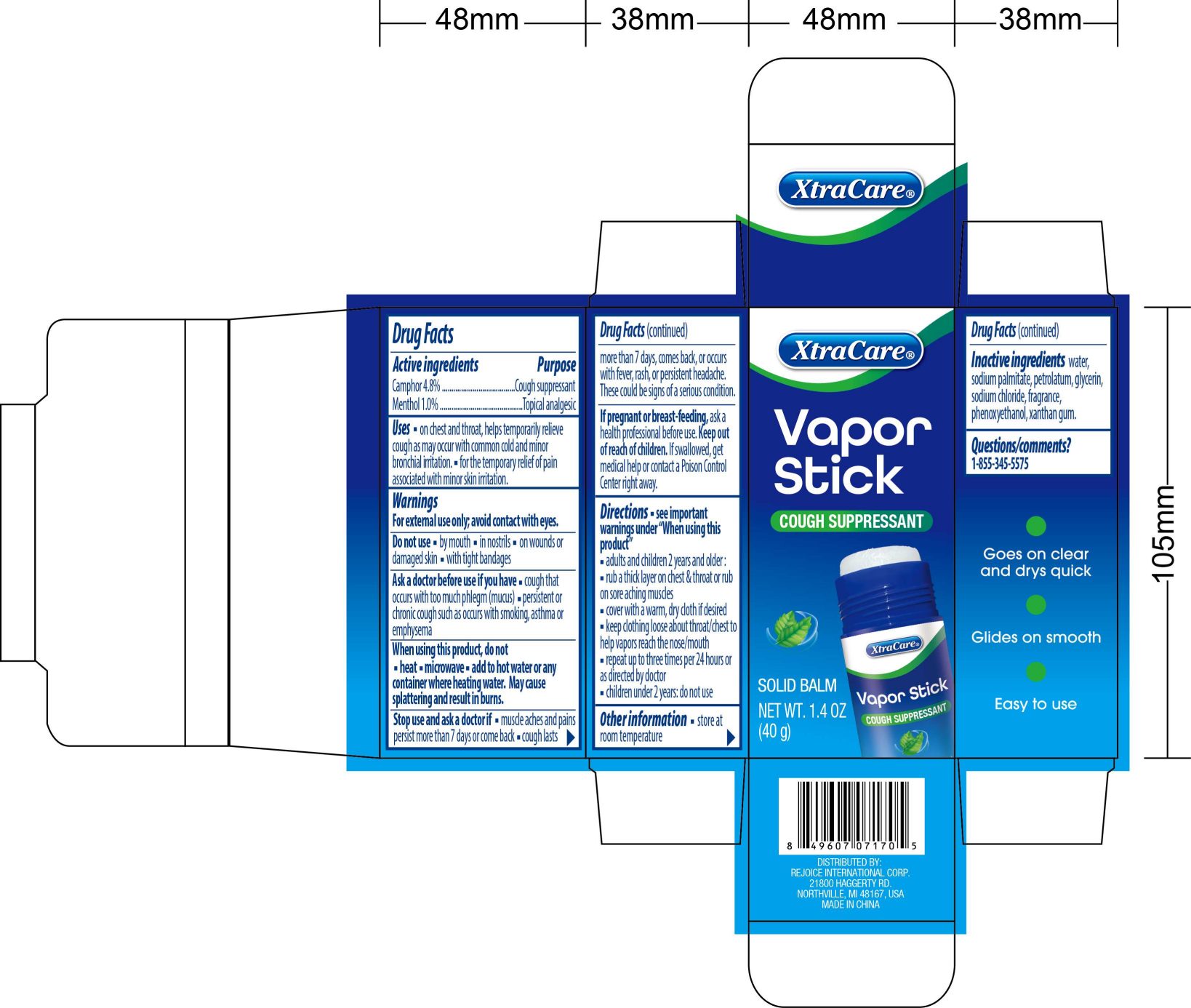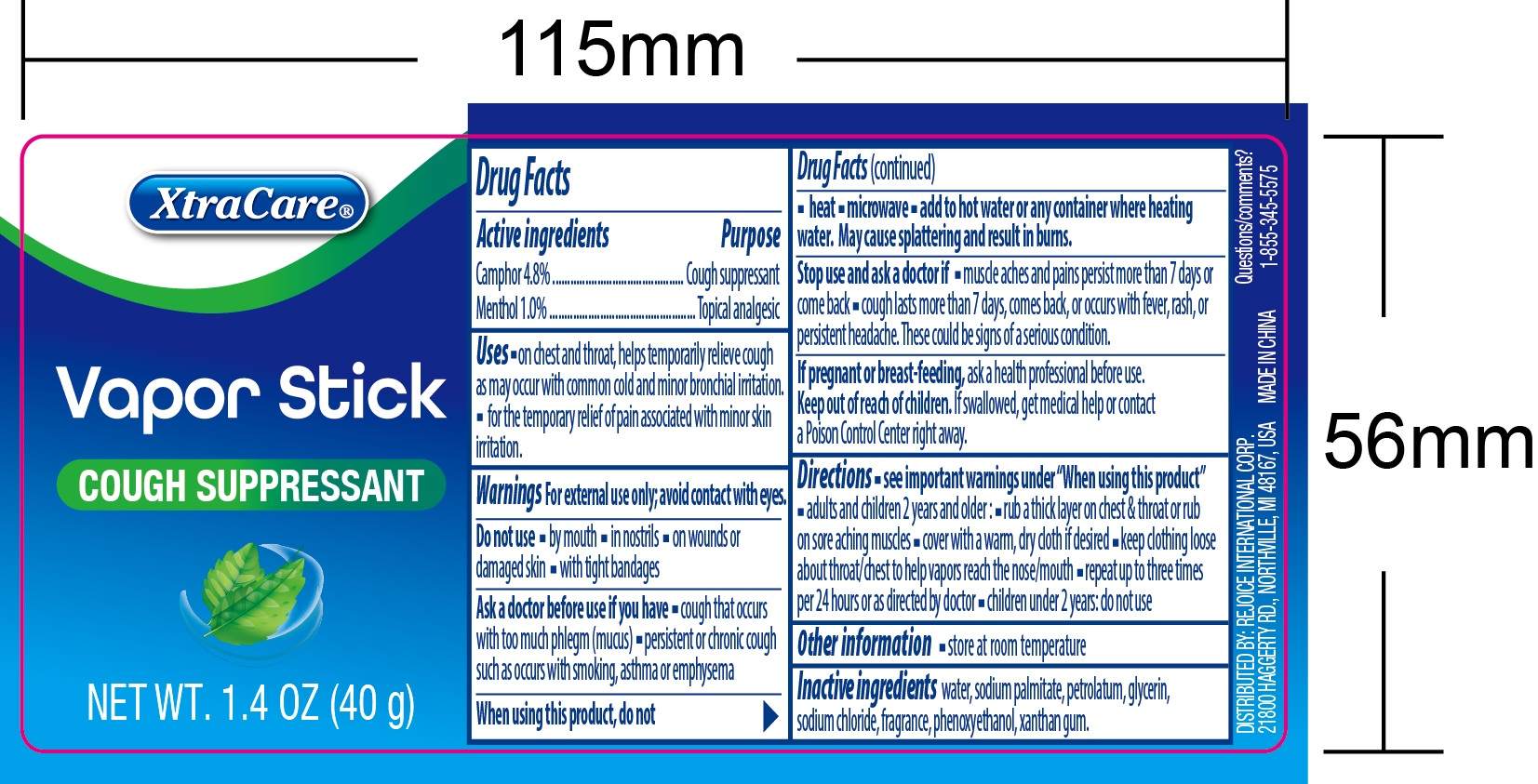 DRUG LABEL: Vapor Stick
NDC: 58503-212 | Form: STICK
Manufacturer: China Ningbo Shangge Cosmetics Technology Corp.
Category: otc | Type: HUMAN OTC DRUG LABEL
Date: 20251023

ACTIVE INGREDIENTS: CAMPHOR (NATURAL) 4.8 g/100 g; MENTHOL 1 g/100 g
INACTIVE INGREDIENTS: PETROLATUM; GLYCERIN; WATER; SODIUM CHLORIDE; SODIUM PALMITATE; XANTHAN GUM; PHENOXYETHANOL

Vapor Stick 1.2oz

Active ingredients

Camphor 4.8%
Menthol 1.0%

Purpose

Cough suppressant
Topical analgesic

Uses

Uses on chest and throat, helps temporarily relieve cough as may occur with common cold and minor bronchial irritation
Uses for the temporary relief of pain associated with minor skin irritation.

Warnings

For external use only; avoid contact with eyes

Do not use by mouth; in nostrils; on wounds or damaged skin; with tight bandages.

Ask a doctor before use if you have cough that occurs with too much phlegm (mucus); persistent or chronic cough such as occurs with smoking, asthma or
emphysema

When using this product

do not heat; microwave ; add to hot water or any container where heating water. May cause splattering and result in burns

Stop use and ask a doctor if muscle asches and pains persist more than days or come back; cough lasts more than 7 days, come back, or occurs with fever, rash, or
persistent headache. These could be signs of a serious condition.

If pregnant or breast-feeding

ask a health professional before use.

Keep out of reach of children

If swallowed, get medical help or contact a Poison Control Center right away.

Directions

see important warnings under :When using this product
adult and children 2 years and older:
rub a thick layer on chest & throat or rub on sore aching muscles
cover with a warm, dry cloth if desired
keep clothing loose about throat/ chest to help vapors reach the nose/ mouth
repeat up to three times per 24 hours or as directed by doctor
children under 2 years: do not use

Other information

Store at room temperature

Inactive ingredients

Water
Sodium Palmitate
Petrolatum
Glycerin
Sodium Chloride
Fragrance
Phenoxyethanol
Xanthan Gum